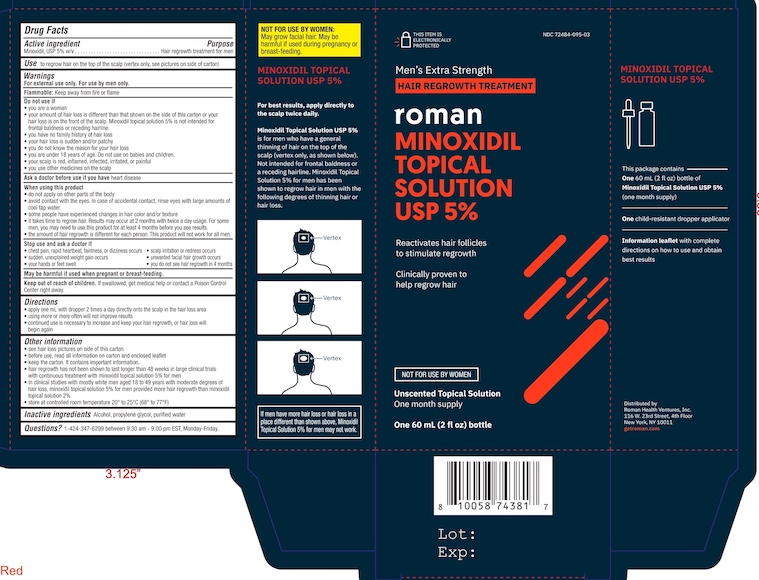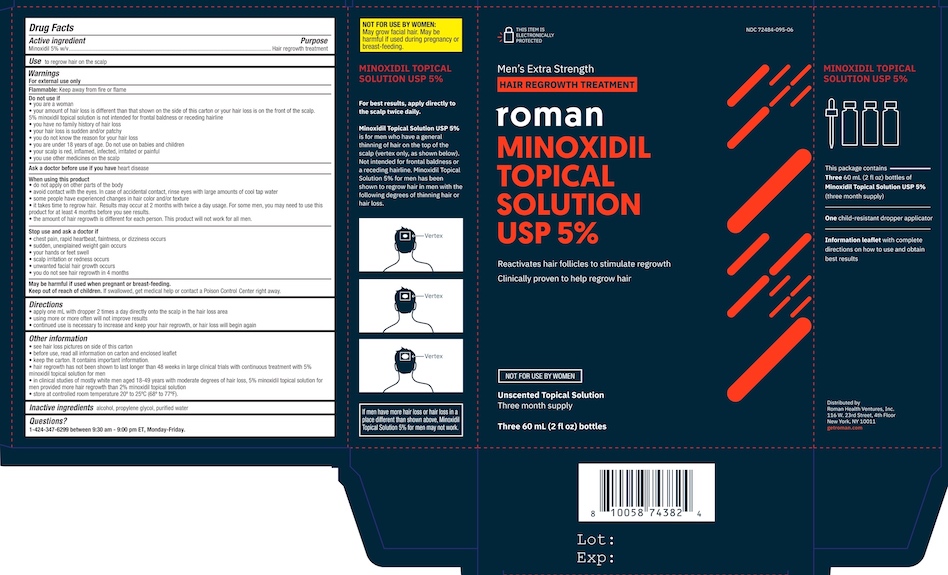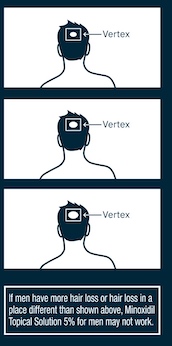 DRUG LABEL: Minoxidil
NDC: 72484-095 | Form: SOLUTION
Manufacturer: Roman Health Ventures Inc.
Category: otc | Type: HUMAN OTC DRUG LABEL
Date: 20250108

ACTIVE INGREDIENTS: MINOXIDIL 5 g/100 mL
INACTIVE INGREDIENTS: ALCOHOL; PROPYLENE GLYCOL; WATER

Minoxidil Topical Solution for Men

Drug Facts

ACTIVE INGREDIENT

1 Bottle Carton

Active ingredient

Minoxidil, USP 5% w/v

3 Bottle Carton

Active ingredient

Minoxidil 5% w/v

PURPOSE

1 Bottle Carton

Purpose

Hair regrowth treatment for men

3 Bottle Carton

Purpose

Hair regrowth treatment

INDICATIONS AND USAGE

1 Bottle Carton

Use to regrow hair on the top of the scalp (vertex only, see pictures on side of carton)

3 Bottle Carton

Use to regrow hair on the scalp

Warnings

For external use only. For use by men only.
Flammable: Keep away from fire or flame

Do not use if

- you are a woman
- your amount of hair loss is different than that shown on the side of this carton or your hair loss is on the front of the scalp. Minoxidil topical solution 5% is not intended for frontal baldness or receding hairline.
- you have no family history of hair loss
- your hair loss is sudden and/or patchy
- you do not know the reason for your hair loss
- you are under 18 years of age. Do not use on babies and children.
- your scalp is red, inflamed, infected, irritated, or painful
- you use other medicines on the scalp

Ask a doctor before use if you have heart disease

When using this product

- do not apply on other parts of the body
- avoid contact with the eyes. In case of accidental contact, rinse eyes with large amounts of cool tap water.
- some people have experienced changes in hair color and/or texture
- it takes time to regrow hair. Results may occur at 2 months with twice a day usage. For some men, you may need to use this product for at least 4 months before you see results.
- the amount of hair regrowth is different for each person. This product will not work for all men.

Stop use and ask a doctor if

- chest pain, rapid heartbeat, faintness, or dizziness occurs
- sudden, unexplained weight gain occurs
- your hands or feet swell
- scalp irritation or redness occurs
- unwanted facial hair growth occurs
- you do not see hair regrowth in 4 months

PREGNANCY OR BREAST FEEDING

May be harmful if used when pregnant or breast-feeding.

Keep out of reach of children. If swallowed, get medical help or contact a Poison Control Center right away.

Directions

- apply one ml with dropper 2 times a day directly onto the scalp in the hair loss area
- using more or more often will not improve results
- continued use is necessary to increase and keep your hair regrowth, or hair loss will begin again

Other information

- see hair loss pictures on side of this carton
- before use, read all information on carton and enclosed leaflet
- keep the carton. It contains important information.
- hair regrowth has not been shown to last longer than 48 weeks in large clinical trials with continuous treatment with minoxidil topical solution 5% for men
- In clinical studies with mostly white men aged 18 to 49 years with moderate degrees of hair loss, minoxidil topical solution 5% for men provided more hair regrowth than minoxidil topical solution 2%
- store at controlled room temperature 20° to 25°C (68° to 77°F)

Inactive ingredients Alcohol, propylene glycol, purified water

QUESTIONS

Questions? 1-424-347-6299 between 9:30 am and 9:00 pm EST, Monday–Friday.

Distributed by

Roman Health Ventures, Inc.

116 W. 23rd Street, 4th Floor

New York, NY 10011

getroman.com

NOT FOR USE BY WOMEN:

May grow facial hair. May be harmful if used during pregnancy or breast-feeding.

For best results, apply directly to scalp twice daily.

Minoxidil Topical Solution USP 5% is for men who have a general thinning of the hair on the top of the scalp (vertex only as shown below). Not intended for frontal baldness or a receding hairline. Minoxidil Topical Solution 5% for men has been shown to regrow hair in men with the following degrees of thinning hair or hair loss.

Single Bottle Package

NDC 72484-095-03
Men's Extra Strength

HAIR REGROWTH TREATMENT

roman MINOXIDIL TOPICAL SOLUTION USP 5%
Reactivates hair follicles to stimulate regrowth
Clinically proven to help regrow hair

NOT FOR USE BY WOMEN
Unscented Topical Solution
One month supply

One 60 mL (2 fl oz) Bottle

Three bottle package

NDC 72484-095-06

Men's Extra Strength

HAIR REGROWTH TREATMENT

roman

MINOXIDIL TOPICAL SOLUTION USP 5%

Reactivates hair follicles to stimulate regrowth

Clinically proven to help regrow hair

NOT FOR USE BY WOMEN

Unscented Topical Solution

Three month supply

Three 60 mL (2 fl oz) bottles